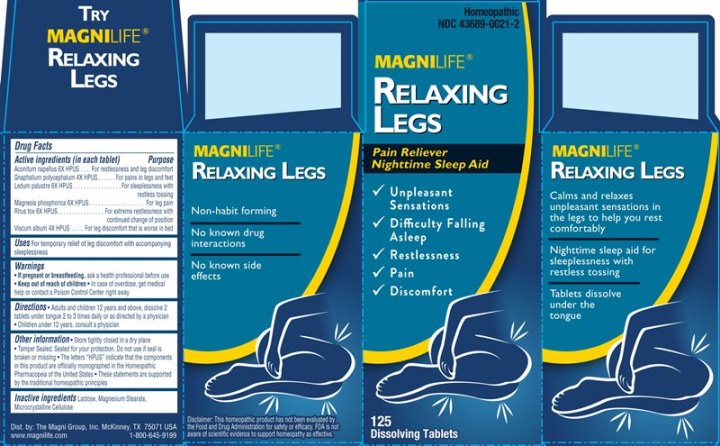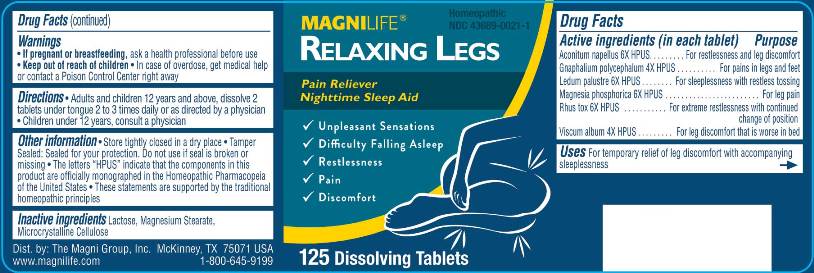 DRUG LABEL: Relaxing Legs
NDC: 43689-0021 | Form: LIQUID
Manufacturer: The Magni Company
Category: homeopathic | Type: HUMAN OTC DRUG LABEL
Date: 20240208

ACTIVE INGREDIENTS: ACONITUM NAPELLUS WHOLE 6 [hp_X]/1 1; PSEUDOGNAPHALIUM OBTUSIFOLIUM WHOLE 4 [hp_X]/1 1; RHODODENDRON TOMENTOSUM LEAFY TWIG 6 [hp_X]/1 1; MAGNESIUM PHOSPHATE, DIBASIC TRIHYDRATE 6 [hp_X]/1 1; TOXICODENDRON PUBESCENS LEAF 6 [hp_X]/1 1; VISCUM ALBUM FRUITING TOP 4 [hp_X]/1 1
INACTIVE INGREDIENTS: LACTOSE; MAGNESIUM STEARATE; CELLULOSE, MICROCRYSTALLINE

DRUG FACTS:

ACTIVE INGREDIENTS:

Aconitum Napellus 6X, Gnaphalium Polycephalum 4X, Ledum Palustre 6X, Magnesia Phosphorica 6X, Rhus Tox, 6X, Viscum Album 4X.

USES:

Temporary relief of leg discomfort with accompanying sleeplessness.

WARNINGS:

• If pregnant or breastfeeding, ask a health professional before use.

• Keep out of reach of children. In case of overdose, get medical help or contact a Poison Control Center right away.

OTHER INFORMATION:

• Store tightly closed in a dry place.

• Tamper sealed: Sealed for your protection. Do not use if seal is broken or missing

• The letters "HPUS" indicate that the components in this product are officially monographed in the Homeopathic Pharmacopeia of the United

States

• These statements are supported by the traditional homeopathic principles

KEEP OUT OF REACH OF CHILDREN:

In case of overdose, get medical help or contact a Poison Control Center right away.

DIRECTIONS:

Adults and children 12 years and above, dissolve 2 tablets under tongue 2 to 3 times daily or as directed by a physician.
Children under 12 years, consult a physician.

INDICATIONS:

Temporary relief of leg discomfort with accompanying sleeplessness.

INACTIVE INGREDIENTS:

Lactose, Magnesium Stearate, Microcrystalline Cellulose

QUESTIONS:

Dist. by: The Magni Group, Inc. McKinney, TX 75071 USA
www.magnilife.com 1-800-645-9199

PACKAGE DISPLAY LABEL:

MAGNILIFE Homeopathic

NDC 43689-0021-1

RELAXING LEGS

Pain Reliever

Nighttime Sleep Aid

√ Unpleasant Sensations

√ Difficulty Falling Asleep

√ Restlessness

√ Pain

√ Discomfort

125 Dissolving Tablets